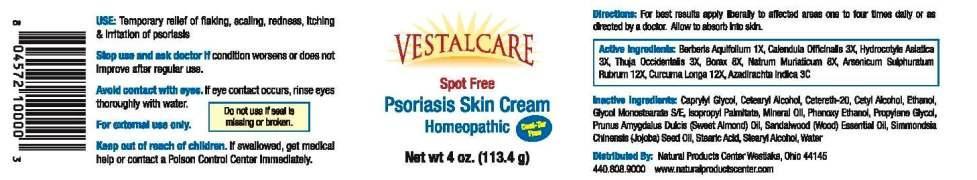 DRUG LABEL: Psoriasis Skin Cream
NDC: 53448-0001 | Form: CREAM
Manufacturer: Natural Products Ctr
Category: homeopathic | Type: HUMAN OTC DRUG LABEL
Date: 20130425

ACTIVE INGREDIENTS: MAHONIA AQUIFOLIUM ROOT BARK 1 [hp_X]/1 g; CALENDULA OFFICINALIS FLOWERING TOP 3 [hp_X]/1 g; CENTELLA ASIATICA 3 [hp_X]/1 g; THUJA OCCIDENTALIS LEAF 3 [hp_X]/1 g; SODIUM BORATE 8 [hp_X]/1 g; SODIUM CHLORIDE 8 [hp_X]/1 g; TETRAARSENIC TETRASULFIDE 12 [hp_X]/1 g; TURMERIC 12 [hp_X]/1 g; AZADIRACHTA INDICA BARK 3 [hp_C]/1 g
INACTIVE INGREDIENTS: WATER; MINERAL OIL; CETYL ALCOHOL; STEARIC ACID; STEARYL ALCOHOL; ISOPROPYL PALMITATE; CETOSTEARYL ALCOHOL; POLYOXYL 20 CETOSTEARYL ETHER; PROPYLENE GLYCOL; ALMOND OIL; GLYCERYL MONOSTEARATE; PHENOXYETHANOL; CAPRYLYL GLYCOL; JOJOBA OIL; SANDALWOOD OIL

Drug Facts

ACTIVE INGREDIENTS

Berberis Aquifolium 1X, Calendula Officinalis 3X, Hydrocotyle Asiatica 3X, Thuja Occidentalis 3X, Borax 8X, Natrum Muriaticum 8X, Arsenicum Sulphuratum Rubrum 12X, Curcuma Longa 12X, Azadirachta Indica 3C

INDICATIONS

Temporary relief of flaking, scaling, redness, itching and irritation of psoriasis.

WARNINGS

Stop use and ask doctor if condition worsens or does not improve after regular use.

Avoid contact with eyes. If eye contact occurs, rinse eyes throughly with water.

For external use only.

Keep out of reach of children. If swallowed, get medical help or contact a Poison Control Center Immediately.

DIRECTIONS

For best results apply liberally to affected areas one to four times daily or as directed by a doctor. Allow to absorb into skin.

INACTIVE INGREDIENTS

Water, Mineral Oil, Cetyl Alcohol, Stearic Acid, Stearyl Alcohol, Isopropyl Palmitate, Cetearyl Alcohol, Cetereth-20, Propylene Glycol, Prunus Amygdalus Duclis (Sweet Almond) Oil, Glycol Monostearate SE, Phenoxy Ethanol, Caprylyl Glycol, Simmondsia Chinensis (Jojoba) Seed Oil

KEEP OUT OF REACH OF CHILDREN

If swallowed, get medical help or contact a Poison Control Center Immediately.

INDICATIONS AND USAGE

Temporary relief of flaking, scaling, redness, itching and irritation of psoriasis.

QUESTIONS

Distributed By: Natural Products Center Westlake, Ohio 44145

440-808-9000 www.naturalproductscenter.com

PACKAGE LABEL

VESTALCARE

Spot Free

Psoriasis Skin Cream

Homeopathic

Net wt 4 oz. (113.4 g)